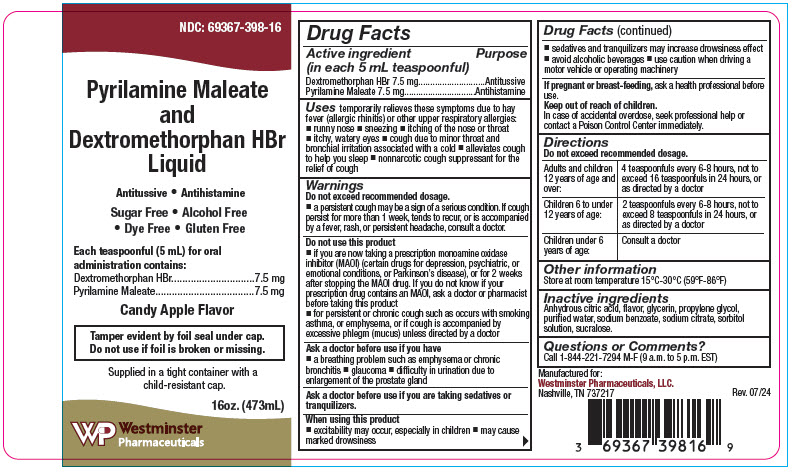 DRUG LABEL: Pyrilamine Maleate and Dextromethorphan Hydrobromide
NDC: 69367-398 | Form: LIQUID
Manufacturer: Westminster Pharmaceuticals, LLC
Category: otc | Type: HUMAN OTC DRUG LABEL
Date: 20240826

ACTIVE INGREDIENTS: DEXTROMETHORPHAN HYDROBROMIDE 7.5 mg/5 mL; PYRILAMINE MALEATE 7.5 mg/5 mL
INACTIVE INGREDIENTS: ANHYDROUS CITRIC ACID; GLYCERIN; PROPYLENE GLYCOL; WATER; SODIUM BENZOATE; SODIUM CITRATE, UNSPECIFIED FORM; SORBITOL; SUCRALOSE

Pyrilamine Maleate and Dextromethorphan Hydrobromide

Drug Facts

ACTIVE INGREDIENT

Active ingredient (in each 5 mL teaspoonful) | Purpose
Dextromethorphan HBr 7.5 mg | Antitussive
Pyrilamine Maleate 7.5 mg | Antihistamine

Uses

temporarily relieves these symptoms due to hay fever (allergic rhinitis) or other upper respiratory allergies:

- runny nose
- sneezing
- itching of the nose or throat
- itchy, watery eyes
- cough due to minor throat and bronchial irritation associated with a cold
- alleviates cough to help you sleep
- nonnarcotic cough suppressant for the relief of cough

Warnings

Do not exceed recommended dosage.

- a persistent cough may be a sign of a serious condition. If cough persist for more than 1 week, tends to recur, or is accompanied by a fever, rash, or persistent headache, consult a doctor.

Do not use this product

- if you are now taking a prescription monoamine oxidase inhibitor (MAOI) (certain drugs for depression, psychiatric, or emotional conditions, or Parkinson's disease), or for 2 weeks after stopping the MAOI drug. If you do not know if your prescription drug contains an MAOI, ask a doctor or pharmacist before taking this product
- for persistent or chronic cough such as occurs with smoking, asthma, or emphysema, or if cough is accompanied by excessive phlegm (mucus) unless directed by a doctor

Ask a doctor before use if you have

- a breathing problem such as emphysema or chronic bronchitis
- glaucoma
- difficulty in urination due to enlargement of the prostate gland

Ask a doctor before use if you are taking sedatives or tranquilizers.

When using this product

- excitability may occur, especially in children
- may cause marked drowsiness
- sedatives and tranquilizers may increase drowsiness effect
- avoid alcoholic beverages
- use caution when driving a motor vehicle or operating machinery

PREGNANCY OR BREAST FEEDING

If pregnant or breast-feeding, ask a health professional before use.

Keep out of reach of children.

In case of accidental overdose, seek professional help or contact a Poison Control Center immediately.

Directions

Do not exceed recommended dosage.

Adults and children 12 years of age and over: | 4 teaspoonfuls every 6-8 hours, not to exceed 16 teaspoonfuls in 24 hours, or as directed by a doctor
Children 6 to under 12 years of age: | 2 teaspoonfuls every 6-8 hours, not to exceed 8 teaspoonfuls in 24 hours, or as directed by a doctor
Children under 6 years of age: | Consult a doctor

Other information

Store at room temperature 15°C-30°C (59°F-86°F)

Inactive ingredients

Anhydrous citric acid, flavor, glycerin, propylene glycol, purified water, sodium benzoate, sodium citrate, sorbitol solution, sucralose.

Questions or Comments?

Call 1-844-221-7294 M-F (9 a.m. to 5 p.m. EST)

PRINCIPAL DISPLAY PANEL - 473 mL Bottle Label

NDC: 69367-398-16

Pyrilamine Maleate
and
Dextromethorphan HBr
Liquid

Antitussive • Antihistamine

Sugar Free • Alcohol Free
• Dye Free • Gluten Free

Each teaspoonful (5 mL) for oral
administration contains:

Dextromethorphan HBr
7.5 mg

Pyrilamine Maleate
7.5 mg

Candy Apple Flavor

Tamper evident by foil seal under cap.
Do not use if foil is broken or missing.

Supplied in a tight container with a
child-resistant cap.

16oz. (473mL)

Westminster
Pharmaceuticals